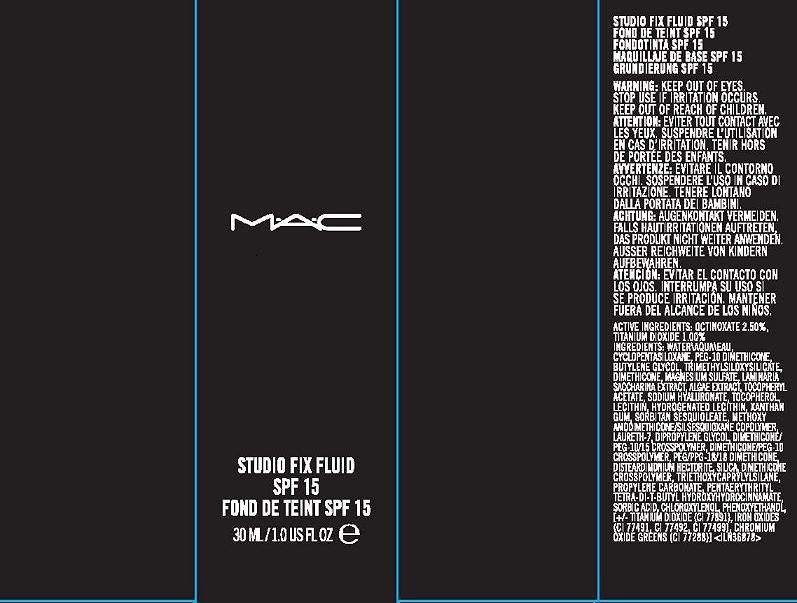 DRUG LABEL: STUDIO FIX FLUID
NDC: 40046-0050 | Form: LOTION
Manufacturer: MAKEUP ART COSMETICS
Category: otc | Type: HUMAN OTC DRUG LABEL
Date: 20110826

ACTIVE INGREDIENTS: OCTINOXATE 2.5 mL/100 mL; TITANIUM DIOXIDE 1 mL/100 mL
INACTIVE INGREDIENTS: WATER; CYCLOMETHICONE 5; BUTYLENE GLYCOL; TRIMETHYLSILANE; DIMETHICONE; MAGNESIUM SULFATE, UNSPECIFIED; SEAWEED; ALPHA-TOCOPHEROL ACETATE; HYALURONATE SODIUM; ALPHA-TOCOPHEROL; LECITHIN, SOYBEAN; HYDROGENATED SOYBEAN LECITHIN; XANTHAN GUM; SORBITAN SESQUIOLEATE; LAURETH-7; DIPROPYLENE GLYCOL; SILICON DIOXIDE; TRIETHOXYCAPRYLYLSILANE; PROPYLENE CARBONATE; PENTAERYTHRITOL TETRAKIS(3-(3,5-DI-TERT-BUTYL-4-HYDROXYPHENYL)PROPIONATE); SORBIC ACID; CHLOROXYLENOL; PHENOXYETHANOL; FERRIC OXIDE RED; CHROMIC OXIDE

ACTIVE INGREDIENT

ACTIVE INGREDIENTS: OCTINOXATE 2.50% [] TITANIUM DIOXIDE 1.00%

INACTIVE INGREDIENT

INACTIVE INGREDIENTS: WATER\AQUA\EAU [] CYCLOPENTASILOXANE [] PEG-10 DIMETHICONE [] BUTYLENE GLYCOL [] TRIMETHYLSILOXYSILICATE [] DIMETHICONE [] MAGNESIUM SULFATE [] LAMINARIA SACCHARINA EXTRACT [] ALGAE EXTRACT [] TOCOPHERYL ACETATE [] SODIUM HYALURONATE [] TOCOPHEROL [] LECITHIN [] HYDROGENATED LECITHIN [] XANTHAN GUM [] SORBITAN SESQUIOLEATE [] METHOXY AMODIMETHICONE/SILSESQUIOXANE COPOLYMER [] LAURETH-7 [] DIPROPYLENE GLYCOL [] DIMETHICONE/PEG-10/15 CROSSPOLYMER [] DIMETHICONE/PEG-10 CROSSPOLYMER [] PEG/PPG-18/18 DIMETHICONE [] DISTEARDIMONIUM HECTORITE [] SILICA [] DIMETHICONE CROSSPOLYMER [] TRIETHOXYCAPRYLYLSILANE [] PROPYLENE CARBONATE [] PENTAERYTHRITYL TETRA-DI-T-BUTYL HYDROXYHYDROCINNAMATE [] SORBIC ACID [] CHLOROXYLENOL [] PHENOXYETHANOL [] [+/- TITANIUM DIOXIDE (CI 77891) [] IRON OXIDES (CI 77491, CI 77492, CI 77499) [] CHROMIUM OXIDE GREENS (CI 77288)]

WARNINGS

WARNING: KEEP OUT OF EYES. STOP USE IF IRRITATION OCCURS. KEEP OUT OF REACH OF CHILDREN

PACKAGE LABEL

PRINCIPAL DISPLAY PANEL

MAC

STUDIO FIX FLUID

SPF 15

1 FL OZ LIQ/ 30 ML

MAKEUP ART COSMETICS

TORONTO, ONTARIO, CANADA M5V 1R7